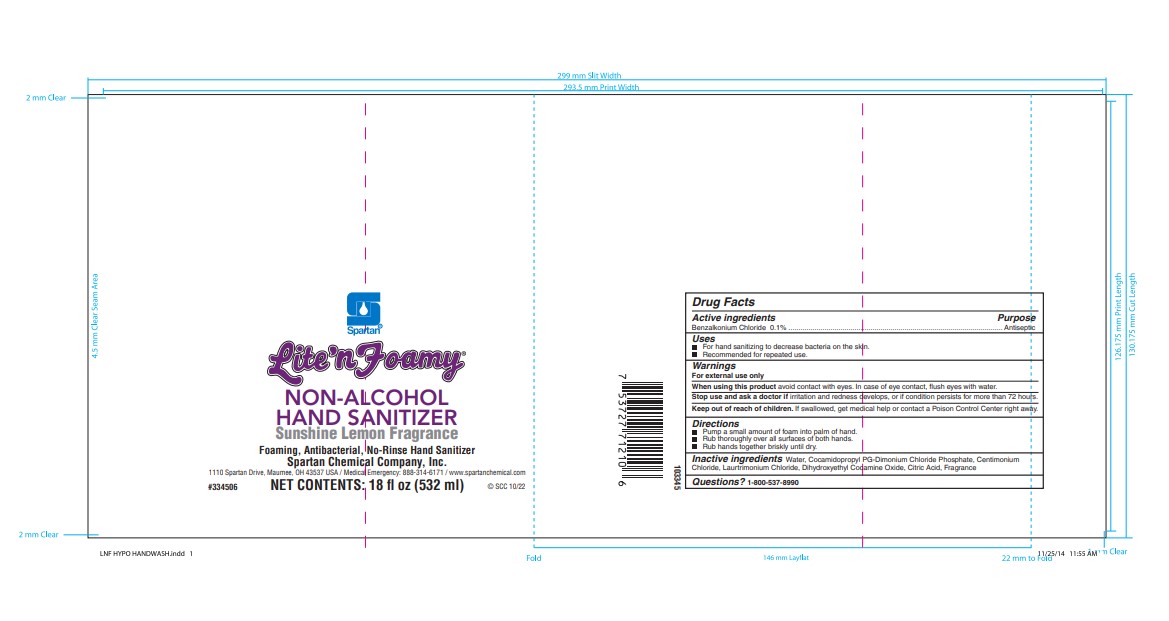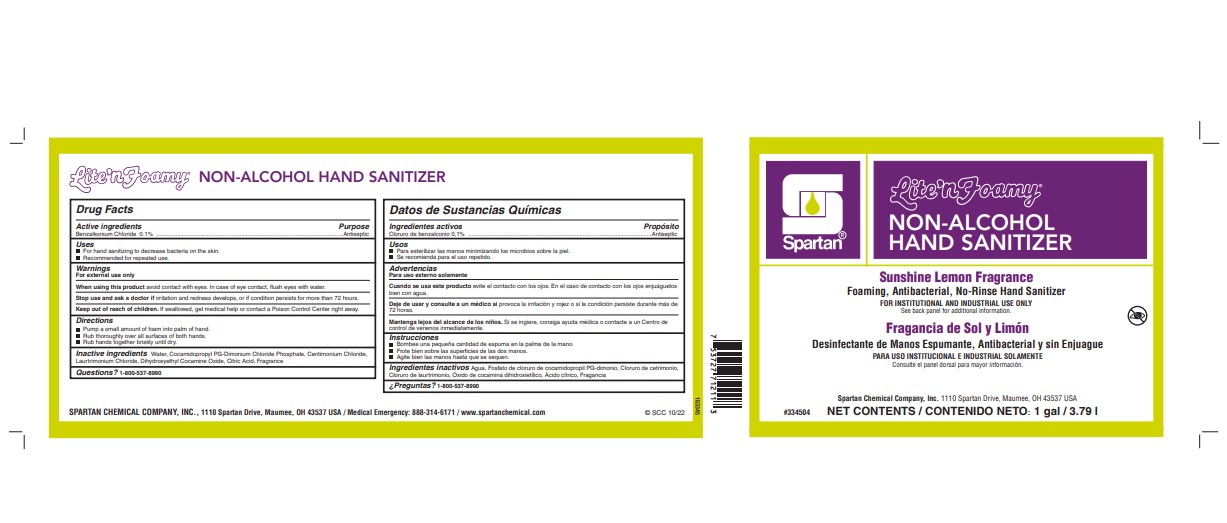 DRUG LABEL: Lite n Foamy Non-Alcohol Hand Sanitizer
NDC: 64009-222 | Form: SOAP
Manufacturer: Spartan Chemical Company
Category: otc | Type: HUMAN OTC DRUG LABEL
Date: 20231219

ACTIVE INGREDIENTS: BENZALKONIUM CHLORIDE 1 g/1000 g
INACTIVE INGREDIENTS: WATER; FRAGRANCE 13576; CITRIC ACID MONOHYDRATE; DIHYDROXYETHYL COCAMINE OXIDE; CETRIMONIUM CHLORIDE; LAURTRIMONIUM CHLORIDE; COCAMIDOPROPYL PG-DIMONIUM CHLORIDE PHOSPHATE

Active Ingredient

Benzalkonium Chloride 0.1% w/w

Purpose

Antiseptic

Use

- For hand sanitizing to decrease bacteria on the skin
- Recommended for repeated use

Warnings

For external use only.

When using this product avoid contact with eyes. In case of eye contact, flush eyes with water.

Stop use and ask a doctor if irritation and redness develops, if condition persists for more than 72 hours consult a doctor.

Keep out of reach of children. If swallowed, get medical help or contact a poison control center right away.

Warnings Section

Keep out of reach of children. If swallowed, get medical help or contact a poison control center right away

Directions

Pump a small amount of foam into palm of hand

Rub thoroughly over all surfaces of both hands

Rub hands together briskly until dry

Inactive Ingredients

Water, Cocomidopropyl PG-Dimonium Chloride Phosphate, Cetrimonium Chloride, Laurtrimonium Chloride, Dihydroxyethyl Cocamine Oxide, Citric Acid, Fragrance

Questions?

1-800-537-8990